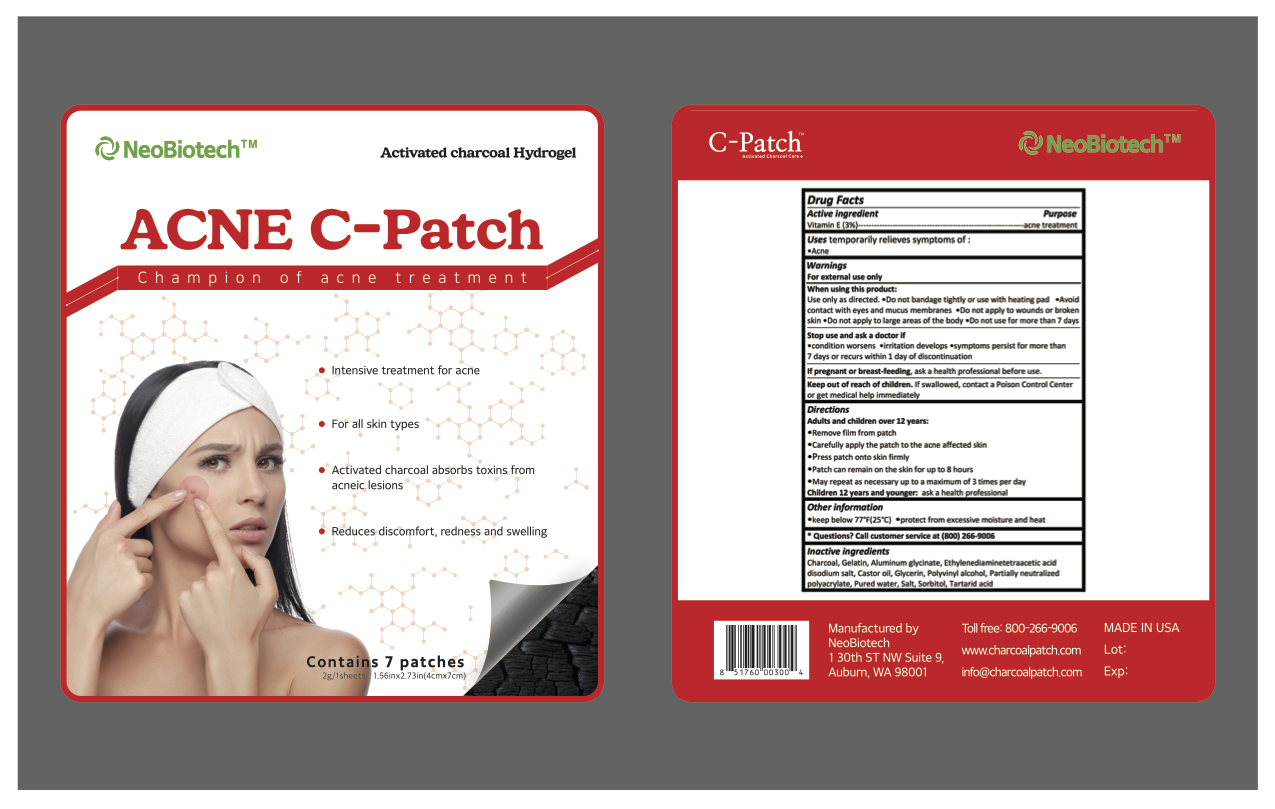 DRUG LABEL: Acne C-Patch
NDC: 70236-103 | Form: PATCH
Manufacturer: NeoBiotech Global Corporation
Category: otc | Type: HUMAN OTC DRUG LABEL
Date: 20180210

ACTIVE INGREDIENTS: .ALPHA.-TOCOPHEROL 0.06 g/2 g
INACTIVE INGREDIENTS: DIHYDROXYALUMINUM AMINOACETATE ANHYDROUS; EDETIC ACID; CASTOR OIL; ACTIVATED CHARCOAL; GELATIN, UNSPECIFIED; TARTARIC ACID; GLYCERIN; POLYVINYL ALCOHOL, UNSPECIFIED; WATER; SODIUM CHLORIDE; SORBITOL

Acne C-Patch

Active ingredients

Vitamin E (3%)

Purpose

acne treatment

USes

temporarily relieves symptoms of

- Acne

Warnings

For external use only

When using this product

Use only as directed.

- Do not bandage tightly or use with heating pad

- Avoid contact with eyes and mucus membranes

- Do not appy wounds or broken skin

- Do not apply to large areas of the body

- In case of deep or puncture wounds, animal bites or serious burns, consult a doctor

Stop use and ask a doctor if

- condition worsen

- irritation develops

- symptoms persist for more than 7 days or recurs within 1 day of discontinuation

- do not use for more than 7 days

If pregnant or breast-feeding, ask a health professional before use

Keep out of reach of children. If swallowd, contact a Poison Control Center or get medical help immediatel

Directions

Adults and children over 12 years:

- Clean affected skin

- Remove film from patch

- Carefully apply the patch to the affected region and press skin firmly

- Patch can remain on the skin for up to 8 hours

- May repeat as necessary up to a maximum of 3 times per day

- For tick and bee stings, remove tick or stinger before applying patch

Children 12 years and younger: ask a health professional

Inactive ingredients

Charcoal, Gelatin, Aluminum glycinate, Ethylennediaminetetraacetic acid, Disodium slat, Castor oil, Polyvinyl alcohol Partially neutralized polyacrylate, Pured water, Salt, Sorbitol, Tartarid acid

Keep out of reach of children. If swallowed, contact a Poison Control Center or get medical help immediately